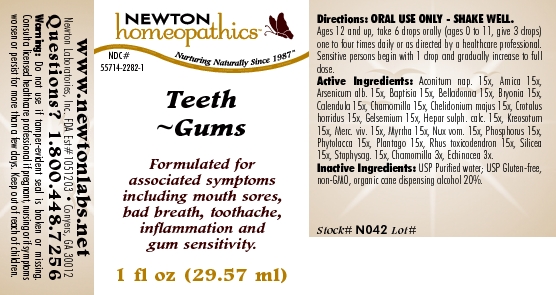 DRUG LABEL: Teeth - Gums 
NDC: 55714-2282 | Form: LIQUID
Manufacturer: Newton Laboratories, Inc.
Category: homeopathic | Type: HUMAN OTC DRUG LABEL
Date: 20110301

ACTIVE INGREDIENTS: Aconitum Napellus 15 [hp_X]/1 mL; Arnica Montana 15 [hp_X]/1 mL; Arsenic Trioxide 15 [hp_X]/1 mL; Baptisia Tinctoria 15 [hp_X]/1 mL; Atropa Belladonna 15 [hp_X]/1 mL; Bryonia Alba Root 15 [hp_X]/1 mL; Calendula Officinalis Flowering Top 15 [hp_X]/1 mL; Matricaria Recutita 15 [hp_X]/1 mL; Chelidonium Majus 15 [hp_X]/1 mL; Crotalus Horridus Horridus Venom 15 [hp_X]/1 mL; Gelsemium Sempervirens Root 15 [hp_X]/1 mL; Calcium Sulfide 15 [hp_X]/1 mL; Wood Creosote 15 [hp_X]/1 mL; Mercury 15 [hp_X]/1 mL; Myrrh 15 [hp_X]/1 mL; Strychnos Nux-vomica Seed 15 [hp_X]/1 mL; Phosphorus 15 [hp_X]/1 mL; Phytolacca Americana Root 15 [hp_X]/1 mL; Plantago Major 15 [hp_X]/1 mL; Toxicodendron Pubescens Leaf 15 [hp_X]/1 mL; Silicon Dioxide 15 [hp_X]/1 mL; Delphinium Staphisagria Seed 15 [hp_X]/1 mL; Echinacea, Unspecified 3 [hp_X]/1 mL
INACTIVE INGREDIENTS: Alcohol

Teeth - Gums

INDICATIONS & USAGE SECTION

Teeth - Gums Formulated for associated symptoms including mouth sores, bad breath, toothache, inflammation and gum sensitivity.

DOSAGE & ADMINISTRATION SECTION

Directions: ORAL USE ONLY - SHAKE WELL. Ages 12 and up, take 6 drops orally (ages 0 to 11, give 3 drops) one to four times daily or as directed by a healthcare professional. Sensitive persons begin with 1 drop and gradually increase to full dose.

OTC - ACTIVE INGREDIENT SECTION

Aconitum nap. 15x, Arnica 15x, Arsenicum alb. 15x, Baptisia 15x, Belladonna 15x, Bryonia 15x, Calendula 15x, Chamomilla 15x, Chelidonium majus 15x, Crotalus horridus 15x, Gelsemium 15x, Hepar sulph. calc. 15x, Kreosotum15x, Merc. viv. 15x, Myrrha 15x, Nux vom. 15x, Phosphorus 15x, Phytolacca 15x, Plantago 15x, Rhus toxicodendron 15x, Silicea 15x, Staphysag. 15x, Chamomilla 3x, Echinacea 3x.

OTC - PURPOSE SECTION

Formulated for associated symptoms including mouth sores, bad breath, toothache, inflammation and gum sensitivity.

INACTIVE INGREDIENT SECTION

Inactive Ingredients: USP Purified Water; USP Gluten-free, non-GMO, organic cane dispensing alcohol 20%.

QUESTIONS SECTION

www.newtonlabs.net Newton Laboratories, Inc. FDA Est # 1051203 - Conyers, GA 30012
Questions? 1.800.448.7256

WARNINGS SECTION

Warning: Do not use if tamper - evident seal is broken or missing. Consult a licensed healthcare professional if pregnant, nursing or if symptoms worsen or persist for more than a few days. Keep out of reach of children.

OTC - PREGNANCY OR BREAST FEEDING SECTION

Consult a licensed healthcare professional if pregnant, nursing or if symptoms worsen or persist for more than a few days.

OTC - KEEP OUT OF REACH OF CHILDREN SECTION

Keep out of reach of children.